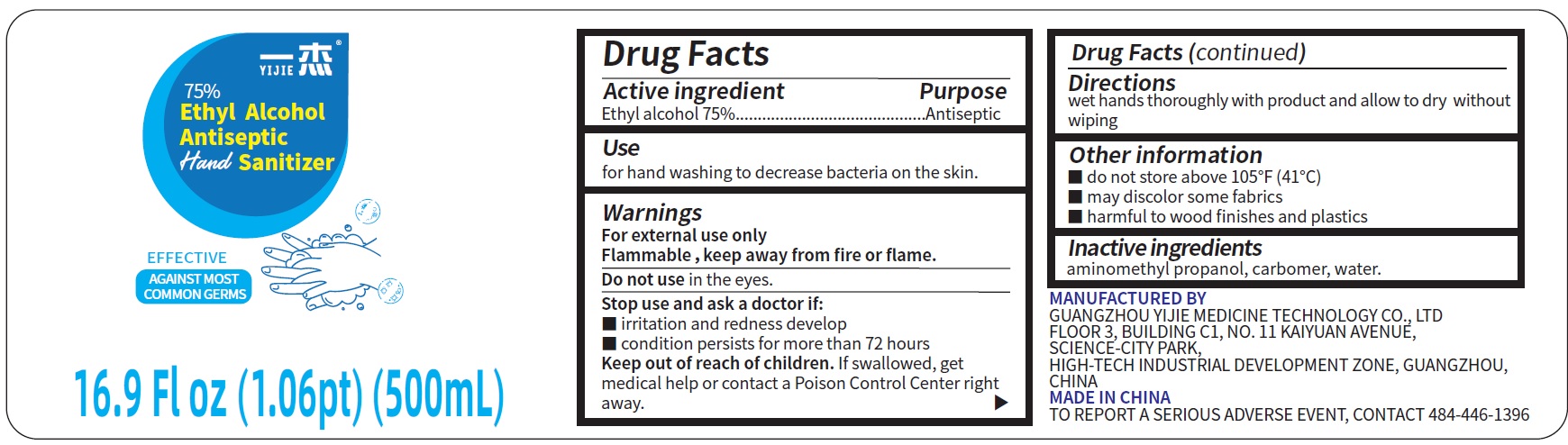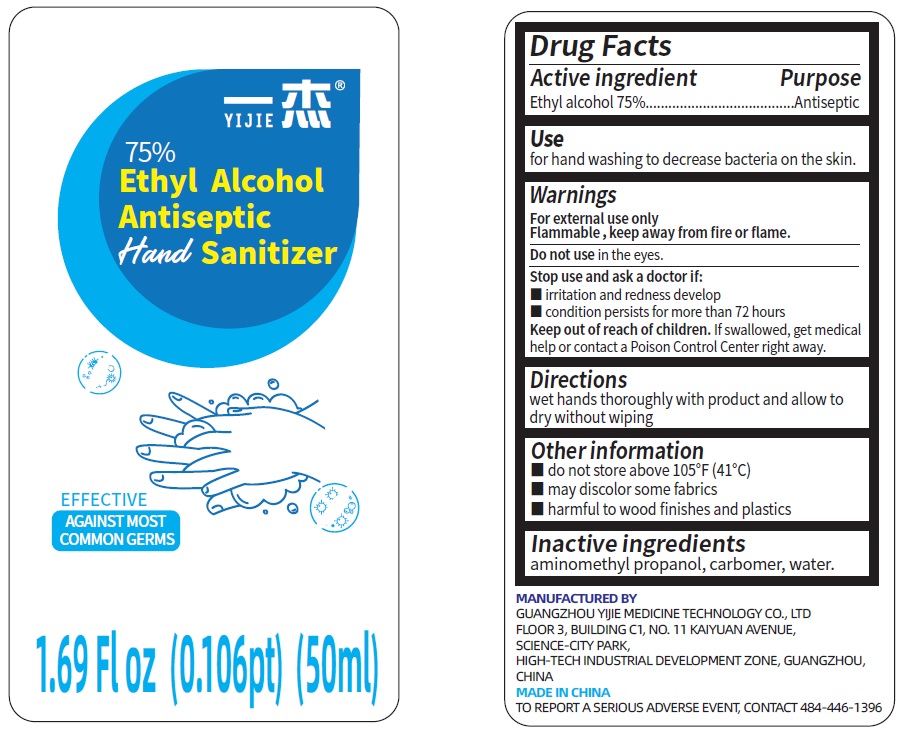 DRUG LABEL: Yijie Ethyl Alcohol Antiseptic Hand Sanitizer
NDC: 75563-000 | Form: GEL
Manufacturer: Guangzhou Yijie Medicine Technology Co., Ltd
Category: otc | Type: HUMAN OTC DRUG LABEL
Date: 20200618

ACTIVE INGREDIENTS: ALCOHOL 0.75 mL/1 mL
INACTIVE INGREDIENTS: AMINOMETHYLPROPANOL; CARBOMER HOMOPOLYMER, UNSPECIFIED TYPE; WATER

Yijie Ethyl Alcohol Antiseptic Hand Sanitizer

Active ingredient

Ethyl alcohol 75%.

Purpose

Antiseptic

Use

for hand washing to decrease bacteria on the skin.

Warnings

For external use only
Flammable ，keep away from fire or flame.

Do not use

in the eyes.

Stop use and ask a doctor if:

- irritation and redness develop
- condition persists for more than 72 hours

Keep out of reach of children.

If swallowed, get medical help or contact a Poison Control Center right away.

Directions

wet hands thoroughly with product and allow to dry without wiping

Other information

- do not store above 105°F (41°C)
- may discolor some fabrics
- harmful to wood finishes and plastics

Inactive ingredients

aminomethyl propanol, carbomer, water.